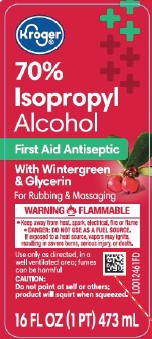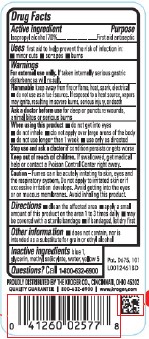 DRUG LABEL: Isopropyl Alcohol
NDC: 30142-845 | Form: LIQUID
Manufacturer: The Kroger Co.
Category: otc | Type: HUMAN OTC DRUG LABEL
Date: 20260210

ACTIVE INGREDIENTS: ISOPROPYL ALCOHOL 70 mL/100 mL
INACTIVE INGREDIENTS: FD&C BLUE NO. 1; GLYCERIN; METHYL SALICYLATE; WATER; FD&C YELLOW NO. 5

Kroger 845.003/845AE
70% IPA, Wintergreen

Active ingredient

Isopropyl alcohol 70%

Purpose

First aid antiseptic

Use

First aid to help prevent the rist of infection in:

- minor cuts
- scrapes
- burns

Warnings

For external use only.If taken internally serious gastric disturbances will result.

Flammable. Keep away from fire or flame, heat, spark, electrical.

- do not use as a fuel source. If exposed to a heat source, vapors may ignite, resulting in severe burns, serious injury, or death.

Ask a doctor before use if

you have deep or puncture wounds, animal bites or serious burns

When using this product

- do not get into eyes
- do not inhale
- do not apply over large areas of the body
- do not use longer than 1 week
- use only as directed

Stop use and ask a doctor if

condition persists or gets worse

Keep out of reach of children.

If swallowed, get medical help or contact a Poison Control Center right away.

Caution

Fumes can be acutely irritating to skin, eyes and the respiratory system. Do not apply to irritated skin or if excessive irritation develops. Avoid getting into the eyes or on mucous membranes. Avoid inhaling this product.

Directions

- clean the affected area
- apply a small amount of this product on the area 1 to 3 times daily
- may be covered with a sterile bandage
- if bandaged, let dry first

Other information

- does not contain, nor is intended as a substitute for grain or ethyl alcohol

Inactive ingredients

blue 1, glycerin, methyl salicylate, water, yellow 5

Questions?

Call 1-800-632-6900

ADVERSE REACTION

DISTRIBUTED BY THE KROGER CO., CINCINNATI, OHIO 45202

QUALTIY GUARANTEE 800-632-6900 www.kroger.com

Pat. D675, 101

principal display panel

Kroger®

70% isopropyl alcohol

First Aid Antiseptic

WITH WINTERGREEN & GLYCERIN

For Rubbing and Massaging

WARNING FLAMMABLE

- Keep away from heat, spark, electrical, fire or flame
- DANGER: DO NOT US AS A FUEL SOURCE.

If exposed to a heat source, vapors may ignite, resulting in severe burns, serious injury, or death.

Use only as directed, in a well-ventilated area; fumes can be harmful

CAUTION: Do not point at self or others; product will squirt when squeezed.

16 FL OZ (1 PT) 473 mL